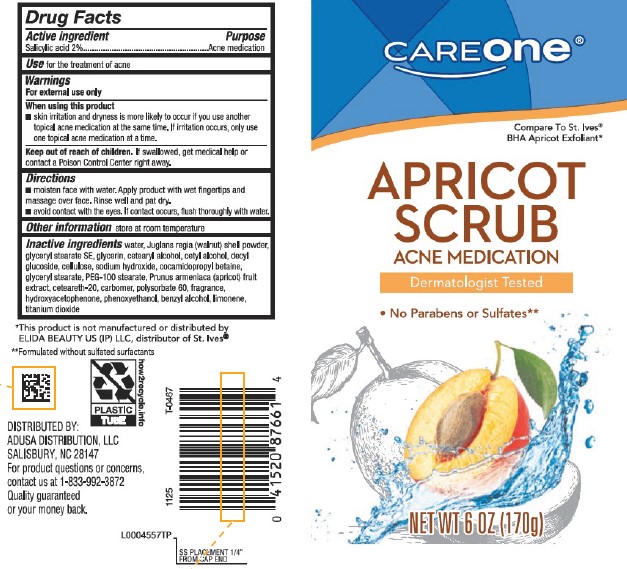 DRUG LABEL: Medicated Apricot Scrub
NDC: 72476-044 | Form: GEL
Manufacturer: Retail Business Services, LLC
Category: otc | Type: HUMAN OTC DRUG LABEL
Date: 20260206

ACTIVE INGREDIENTS: SALICYLIC ACID 20 mg/1 g
INACTIVE INGREDIENTS: WATER; JUGLANS REGIA SHELL; GLYCERYL STEARATE SE; GLYCERIN; CETOSTEARYL ALCOHOL; CETYL ALCOHOL; DECYL GLUCOSIDE; POWDERED CELLULOSE; SODIUM HYDROXIDE; COCAMIDOPROPYL BETAINE; GLYCERYL MONOSTEARATE; PEG-100 STEARATE; APRICOT; POLYOXYL 20 CETOSTEARYL ETHER; CARBOMER HOMOPOLYMER, UNSPECIFIED TYPE; POLYSORBATE 60; HYDROXYACETOPHENONE; PHENOXYETHANOL; BENZYL ALCOHOL; LIMONENE, (+)-; TITANIUM DIOXIDE

Care One 041.008/041AM
Medicated Apricot Scrub

Active ingredient

Salicylic acid 2%

Purpose

Acne medication

Use

for the treatment of acne

Warnings

For external use only

When using this product

- skin irritation and dryness is more likely to occure if you use another topical acne medication at the same time. If irritation occurs, only use one topical acne medication at a time.

Keep out of reach of children.

If swallowed, get medical help or contact a Poison Control Center right away.

Directions

- moisten face with water. Apply product with wet fingertips and massage over face. Rinse well and pat dry.
- avoid contact with the eyes. If contact occurs, flush thoroughly with water.

Other information

store at room temperature

Inactive ingredients

water, Juglans regia (walnut) shell powder, glyceryl stearate SE, glycerin, cetearyl alcohol, cetyl alcohol, decyl glucoside, cellulose, sodium hydroxide, cocamidopropyl betaine, glyceryl stearate, PEG-100 stearate, Prunus armeniaca (apricot) fruit extract, ceteareth-20, carbomer, polysorbate 60, fragrance, hydroxyacetophenone, phenoxyethanol, benzyl alcohol, limonene, titanium dioxide

Disclaimer

*This product is not manufactured or distributed by ELIDA BEAUTY US (IP) LLC, distributor of St. Ives® .

**Formulated without sulfated surfactants

ADVERSE REACTION

DISTRIBUTED BY:

ADUSA DISTRIBUTION, LLC

SALISBURY, NC 28147

For product questions or concerns, contact us at 1-833-992-3872.

Quality guaranteed or your money back.

PLASTIC TUBE

how2recycle.info

Principal display panel

CAREone®

Compare to St. Ives® BHAl Apricot Exfoliant*

APRICOT SCRUB

ACNE MEDICATION

Dermatologist Tested

- No Paraben or Sulfates**

NET WT 6 0Z (170 g)